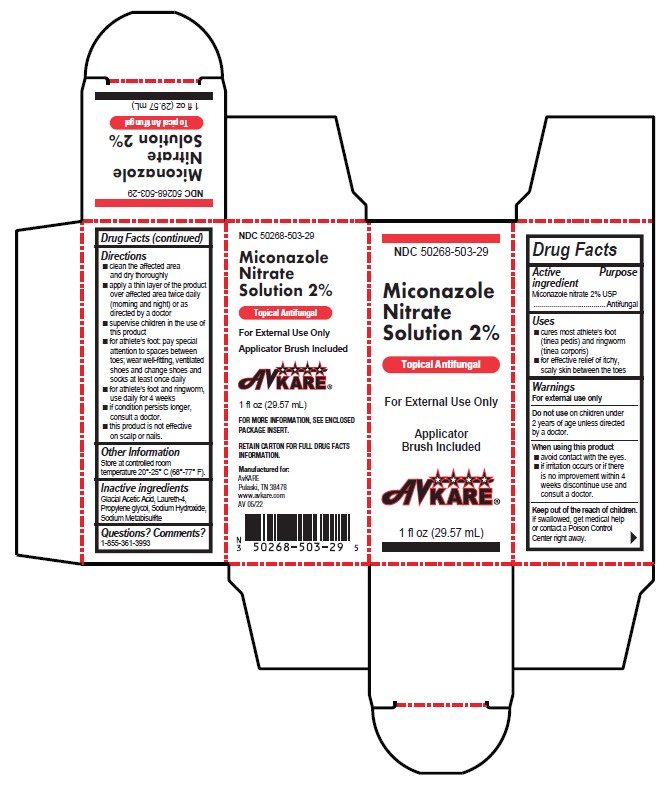 DRUG LABEL: miconazole nitrate
NDC: 50268-503 | Form: SOLUTION
Manufacturer: AvPAK
Category: otc | Type: HUMAN OTC DRUG LABEL
Date: 20240306

ACTIVE INGREDIENTS: MICONAZOLE NITRATE 20 mg/1 mL
INACTIVE INGREDIENTS: PROPYLENE GLYCOL; ACETIC ACID; LAURETH-4; SODIUM HYDROXIDE; SODIUM METABISULFITE

Miconazole Nitrate 2% Solution
Topical Antifungalk

Drug Facts

Active Ingredient

Miconazole Nitrate 2%

Inactive Ingredients

Glacial Acetic Acid, Laureth-4, Propylene glycol, Sodium Hydroxide, Sodium Metabisulfite

Purpose

Topical Antifungal

Uses

Cures most athlete’s foot (tinea pedis) and ring worm (tinea corporis). Under professional supervision, Miconazole Nitrate
2% Solution can be used for the treatment of superficial skin infections caused by yeast (Candida albicans).

WARNINGS

DO NOT USE ON CHILDREN UNDER TWO YEARS OF AGE EXCEPT UNDER THE ADVICE AND SUPERVISION OF A
DOCTOR. FOR EXTERNAL USE ONLY. KEEP OUT OF THE REACH OF CHILDREN. In case of accidental ingestion, seek professional assistance or contact Poison Control Center immediately. Avoid contact with eyes. If irritation occurs or if there is no improvement within four weeks, discontinue use and consult a doctor or pharmacist. Do not use if you are diabetic or have circulatory, renal, or hepatic problems, consult a doctor or pharmacist before using.

Directions

Cleanse and dry affected areas. Apply a thin application twice a day (morning and night) on skin under nails and surrounding
cuticle areas or as recommended by your doctor or pharmacist. Remove Miconazole Nitrate 2% Solution from any untreated areas.
Remove from all inanimate environmental surfaces. Supervise children in the use of this product. For athlete’s foot, pay special attention to the spaces between the toes; wear well fitting, ventilated shoes and change shoes and socks at least once a day. For athlete’s foot and ringworm use daily for 4 weeks. For fungal infections of the nail bed, if conditions persist, consult a doctor who may choose to debride or remove the nail to allow application of Miconazole Nitrate 2% Solution to the skin of the nail bed. This product is not effective on the scalp or nails.

Other Information

Store at 20°C to 25°C (68°F to 77°F), excursions permitted between 15°C and 30°C (between 59°F and 86°F). Brief exposure to temperatures up to 40°C (104°F) may be tolerated provided the mean kinetic temperature does not exceed 25°C (77°F); however, such exposure should be minimized. [See USP Controlled Room Temperature]. Protect from freezing. If freezing occurs, warm to room temperature.
For product questions, or to report a serious adverse event, call 1-855-361-3993.

Regardless of your level of personal hygiene, your skin can be covered with microscopic organisms, including molds and yeast like fungi. While most microorganisms are not harmful, some can invade your skin and
cause an infection.

FUNGUS TYPES:
Mold-like fungi called dermatophytes cause athlete’s foot, jock itch, and ringworm of the skin or scalp. These fungi live on dead tissue of your hair, nails, and the outer layer of your skin. Poor hygiene, continually moist skin, and minor skin or nail injuries increase your chances of developing a fungal infection.

Athlete’s Foot and Jock Itch: Athlete’s foot and jock itch are skin conditions caused by fungi that thrive in warm, moist areas. In all cases, itching and rash are the most noticeable symptoms. Athlete’s foot produces itching, stinging, and burning on the soles of the feet, palms and between fingers and toes. Cracking and peeling of the skin may occur as well. Jock itch consists of itching in the groin and anal areas.

Ringworm: Most common in children, ringworm causes a ringshaped pattern on the skin or scalp that grow outward as the infection
spreads. The ring itself is the most actively infected area, while the skin inside the ring is less actively infected. Ringworm is very contagious and can be passed from shared hats, combs or brushes and barber tools. Ringworm infections can also develop from contact with pets or domestic animals. To treat the infection, wash the area and dry thoroughly. Apply a thin layer of Miconazole Nitrate 2% Solution twice a day (morning and evening) over the affected area or as recommended by a doctor. Use daily for 4 weeks.

PREVENTIONS AND TREATMENT:
Athlete’s Foot and Jock Itch: Good personal hygiene is essential in preventing or treating athlete’s foot and jock itch. To prevent athlete’s foot, wear well-fitting, well-ventilated shoes and change shoes and socks at least once a day. For treatment, apply Miconazole Nitrate 2% Solution twice daily (morning and evening) or as directed by a doctor and pay special attention to the areas between toes. Apply twice a day on skin under nails and surrounding cuticle areas. Continue treatment twice a day for 4 weeks. To prevent jock itch, keep the groin and anal areas clean and dry, avoid chaffing and launder athletic supports frequently. For
treatment, use Miconazole Nitrate 2% Solution in the same manner over the affected area. Continue treatment for 2 weeks.

Fingernails and Toenails-General Information: Your nails are produced from cells in the tips of your fingers and toes and are composed of laminated layers a protein called “Keratin”. Each nail grows towards the end of your finger or toe from a nail root that extends back into a groove of skin. Just in front of your nail root is your cuticle skin, which is attached to the nail surface and helps protect the new keratin cells that slowly emerge from below. The following lists conditions that may develop in your nails
and how to take proper care of your nails.

Paronychia Signs and Symptoms: (Red swollen area on the skin next to a nail): Paronychia is a superficial infection of the skin around the nail, most commonly caused by either staphylococci or yeast. Superficial pus blisters may appear. Pressing the affected area can produce oozing pus. Paronychia may also be caused by fungal infections and is common among those with diabetes mellitus and those who may have their hands in water for long periods. Like other fungal infections, paronychia may develop slowly, but prove to be very persistent. To treat the infection, soak the affected area in clean, warm water. This will help decrease
inflammation of the tissues. After soaking, apply an antibacterial or antifungal agent to the affected area. Consult a doctor if you are not sure whether a paronychia infection is bacterial or fungal.

Fungal Infections of the Nails: Fungus spores may attach themselves to the dense bed of keratin cells that make up your nails. These microscopic organisms can then digest the keratin and live within it. The resulting infection is called Onychomycosis (tinea of the nails), may persist indefinitely. It can cause nails to thicken, discolor, become lusterless and crumble along the edges. Onychomycosis can be contracted by walking barefoot in public places or may develop as a complication of athlete’s foot. The associated infection of the foot or hand may be mild, producing no inflammation, or it may be acute, accompanied by blisters
and painful swelling. Once the nails become involved, they may even become detached and shed and may be entirely destroyed. Consult a doctor if you suspect an Onychomycosis infection. A simple test can identify the fungus and rule out other diseases of the nails. A topical antifungal solution, such as Miconazole Nitrate 2% Solution can treat the skin under the nails and surrounding cuticle area but will not penetrate the nails themselves. If you have a fungal infection that is disabling or excessively disfiguring, consult your doctor to find out the best treatment for you.

GENERAL INFORMATION About Miconazole Nitrate 2% Solution:
Important Tips on Using Miconazole Nitrate 2% Solution:
Use Miconazole Nitrate 2% Solution as soon as an infection is detected. This will kill the fungus before it gets out of control and prevents it from spreading to other areas.

HOW SUPPLIED

NDC# 50268-503-29
1 fl. oz. (29.57mL) bottle with brush applicator containing an alcohol-free clear solution.

For more information, see enclosed package insert.

Questions?

FREQUENTLY ASKED QUESTIONS:
What is the active ingredient in Miconazole Nitrate 2% Solution?
Miconazole Nitrate 2% Solution contains 2% miconazole nitrate, the maximum strength antifungal allowed by the FDA without a prescription.

Do I apply Miconazole Nitrate 2% Solution to the nail?
No, nothing penetrates nails. Fungus is not growing on the nail but on the nail bed (skin). Apply Miconazole Nitrate 2% Solution on skin under nails and surrounding cuticle areas twice a day (morning and evening).

When can I expect results?
You may start seeing results in as little as 4 to 6 weeks.

How long does it take for a nail to grow?
It could take 8 to 10 months for a nail to grow out completely.

Why does your package say: “This product is not effective on the scalp or nails”?
In 1994, the FDA ruled that no over-the-counter antifungal product is effective on the nails. The FDA’s opinion was that antifungal products available without a prescription could not penetrate the nails and are therefore, ineffective in treating them. The statement “this product is not effective on scalp or nails” was subsequently required on the labels of all over-the-counter antifungal products. Fungus is an infection of the skin, not the nail.

Can I use Miconazole Nitrate 2% Solution for Athlete’s Foot?
Yes, Miconazole Nitrate 2% Solution is a potent antifungal. It treats athlete’s foot and ringworm. For athlete’s foot and ringworm, apply Miconazole Nitrate 2% Solution to the affected area twice a day for 4 weeks; pay special attention to spaces between the toes.

Can children use Miconazole Nitrate 2% Solution?
Miconazole Nitrate 2% Solution is safe and effective for children over 2 years of age. Children under 2 years of age, use only under physician supervision.

What happens if Miconazole Nitrate 2% Solution spills?
Care should be taken to avoid spilling because Miconazole Nitrate 2% Solution may damage counter tops, porcelain, stainless steel, flooring, etc.

For product questions, or to report a serious adverse event, call 1-855-361-3993.

AvKARE, Pulaski, TN 38478
www.avkare.com
AV 07/2022